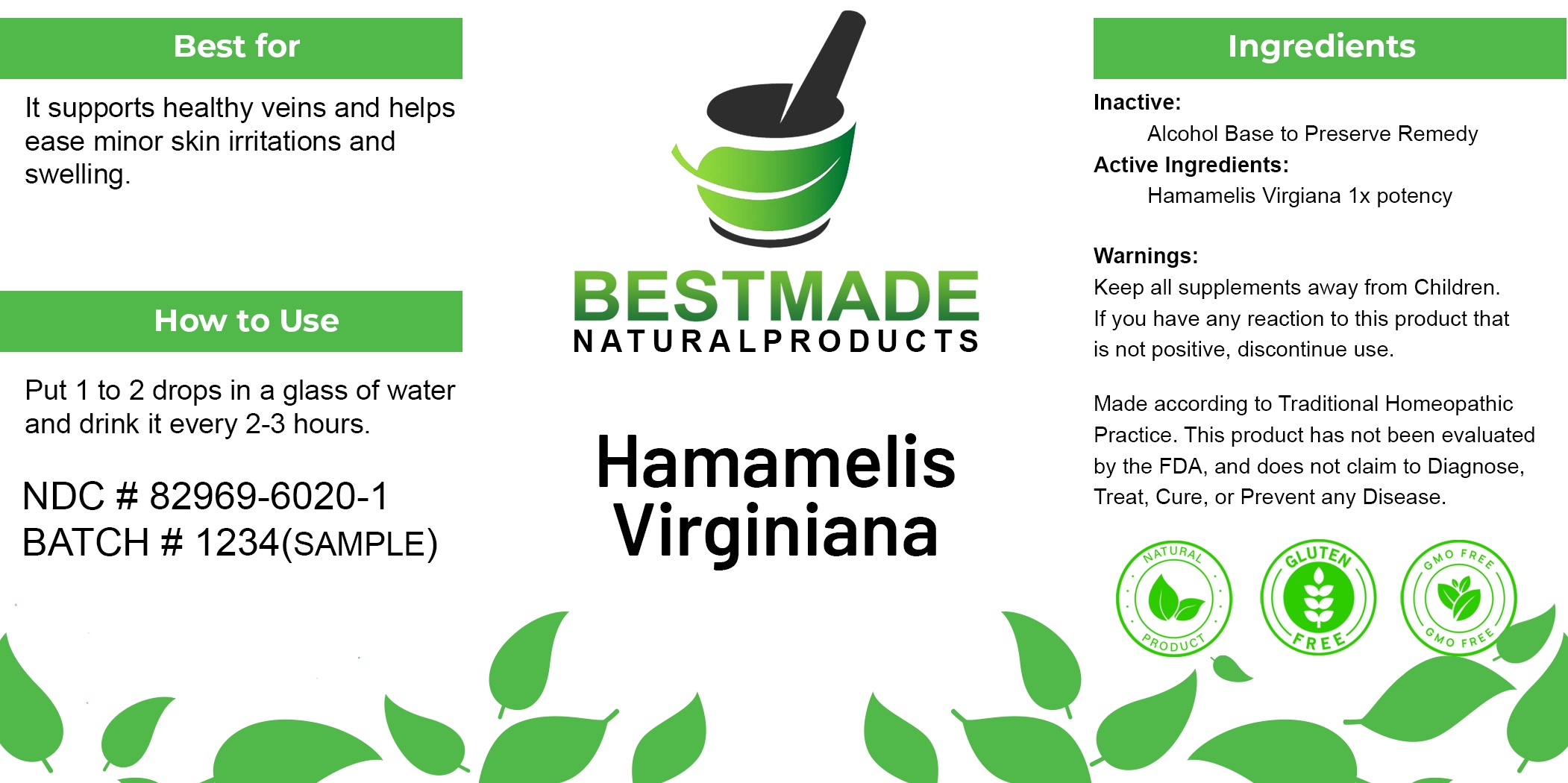 DRUG LABEL: Hamamelis Virgiana
NDC: 82969-6020 | Form: TINCTURE
Manufacturer: Bestmade Natural Products
Category: homeopathic | Type: HUMAN OTC DRUG LABEL
Date: 20250102

ACTIVE INGREDIENTS: HAMAMELIS VIRGINIANA LEAF 1 [hp_X]/30 mL
INACTIVE INGREDIENTS: ALCOHOL 30 mL/30 mL

Hamamelis Virgiana Tincture

DOSAGE AND ADMINISTRATION

How to Use
Put 1 to 2 drops in a glass of water and drink it every 2-3 hours.

INDICATIONS AND USAGE

Best for
It supports healthy veins and helps ease minor skin irritations and swelling.

PURPOSE

Best for
It supports healthy veins and helps ease minor skin irritations and swelling.

INACTIVE INGREDIENT

Ingredients
Inactive:
Alcohol Base to Preserve Remedy

Warnings:
Keep all supplements away from Children.
If you have any reaction to this product that is not positive, discontinue use.

Made according to Traditional Homeopathic Practice. This product has not been evaluated by the FDA, and does not claim to Diagnose, Treat, Cure, or Prevent any Disease.

Warnings:
Keep all supplements away from Children.
If you have any reaction to this product that is not positive, discontinue use.

Made according to Traditional Homeopathic Practice. This product has not been evaluated by the FDA, and does not claim to Diagnose, Treat, Cure, or Prevent any Disease.

Active Ingredients:
Hamamelis Virginiana 1x potency

entire package label